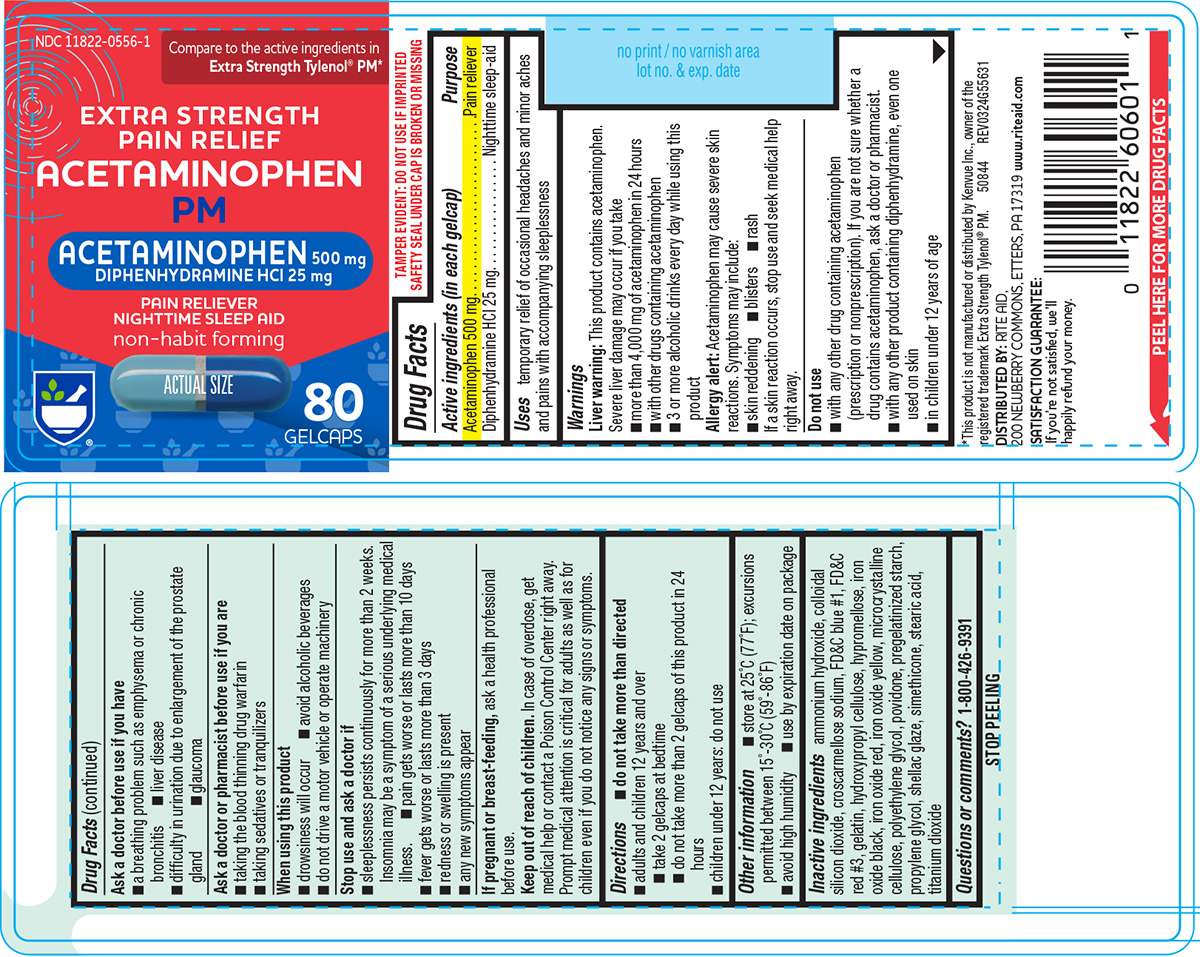 DRUG LABEL: Pain Relief Acetaminophen PM
NDC: 11822-0556 | Form: TABLET, COATED
Manufacturer: Rite Aid Corporation
Category: otc | Type: HUMAN OTC DRUG LABEL
Date: 20260105

ACTIVE INGREDIENTS: ACETAMINOPHEN 500 mg/1 1; DIPHENHYDRAMINE HYDROCHLORIDE 25 mg/1 1
INACTIVE INGREDIENTS: AMMONIA; SILICON DIOXIDE; CROSCARMELLOSE SODIUM; FD&C BLUE NO. 1; FD&C RED NO. 3; GELATIN, UNSPECIFIED; HYDROXYPROPYL CELLULOSE, UNSPECIFIED; HYPROMELLOSE, UNSPECIFIED; FERROSOFERRIC OXIDE; FERRIC OXIDE RED; FERRIC OXIDE YELLOW; MICROCRYSTALLINE CELLULOSE; POLYETHYLENE GLYCOL, UNSPECIFIED; POVIDONE, UNSPECIFIED; STARCH, CORN; PROPYLENE GLYCOL; SHELLAC; STEARIC ACID; TITANIUM DIOXIDE

Rite Aid 44-556

Active ingredients (in each gelcap)

Acetaminophen 500 mg
Diphenhydramine HCl 25 mg

Purpose

Pain reliever
Nighttime sleep-aid

Uses

temporary relief of occasional headaches and minor aches and pains with accompanying sleeplessness

Warnings

Liver warning: This product contains acetaminophen. Severe liver damage may occur if you take

- more than 4,000 mg of acetaminophen in 24 hours
- with other drugs containing acetaminophen
- 3 or more alcoholic drinks every day while using this product

Allergy alert: Acetaminophen may cause severe skin reactions. Symptoms may include:

- skin reddening
- blisters
- rash

If a skin reaction occurs, stop use and seek medical help right away.

Do not use

- with any other drug containing acetaminophen (prescription or nonprescription). If you are not sure whether a drug contains acetaminophen, ask a doctor or pharmacist.
- with any other product containing diphenhydramine, even one used on skin
- in children under 12 years of age

Ask a doctor before use if you have

- a breathing problem such as emphysema or chronic bronchitis
- liver disease
- difficulty in urination due to enlargement of the prostate gland
- glaucoma

Ask a doctor or pharmacist before use if you are

- taking the blood thinning drug warfarin
- taking sedatives or tranquilizers

When using this product

- drowsiness will occur
- avoid alcoholic beverages
- do not drive a motor vehicle or operate machinery

Stop use and ask a doctor if

- sleeplessness persists continuously for more than 2 weeks. Insomnia may be a symptom of a serious underlying medical illness.
- any new symptoms appear
- redness or swelling is present
- pain gets worse or lasts more than 10 days
- fever gets worse or lasts more than 3 days

If pregnant or breast-feeding,

ask a health professional before use.

Keep out of reach of children.

In case of overdose, get medical help or contact a Poison Control Center right away. Prompt medical attention is critical for adults as well as for children even if you do not notice any signs or symptoms.

Directions

- do not take more than directed
- adults and children 12 years and over
  - take 2 gelcaps at bedtime
  - do not take more than 2 gelcaps of this product in 24 hours
- children under 12 years: do not use

Other information

- store at 25°C (77°F); excursions permitted between 15°-30°C (59°-86°F)
- avoid high humidity
- use by expiration date on package

Inactive ingredients

ammonium hydroxide, colloidal silicon dioxide, croscarmellose sodium, FD&C blue #1, FD&C red #3, gelatin, hydroxypropyl cellulose, hypromellose, iron oxide black, iron oxide red, iron oxide yellow, microcrystalline cellulose, polyethylene glycol, povidone, pregelatinized starch, propylene glycol, shellac glaze, simethicone, stearic acid, titanium dioxide

Questions or comments?

1-800-426-9391

Principal Display Panel

NDC 11822-0556-1

Compare to the active ingredients in
Extra Strength Tylenol® PM*

EXTRA STRENGTH
PAIN RELIEF
ACETAMINOPHEN
PM

ACETAMINOPHEN 500 mg
DIPHENHYDRAMINE HCl 25 mg

PAIN RELIEVER
NIGHTTIME SLEEP AID
non-habit forming

ACTUAL SIZE

80
GELCAPS

TAMPER EVIDENT: DO NOT USE IF IMPRINTED
SAFETY SEAL UNDER CAP IS BROKEN OR MISSING

*This product is not manufactured or distributed by Kenvue Inc., owner of the
registered trademark Extra Strength Tylenol® PM. 50844 REV0324G55631

DISTRIBUTED BY: RITE AID,
200 NEWBERRY COMMONS, ETTERS, PA 17319 www.riteaid.com

SATISFACTION GUARANTEE:
If you’re not satisfied, we’ll
happily refund your money.

Rite Aid 44-556